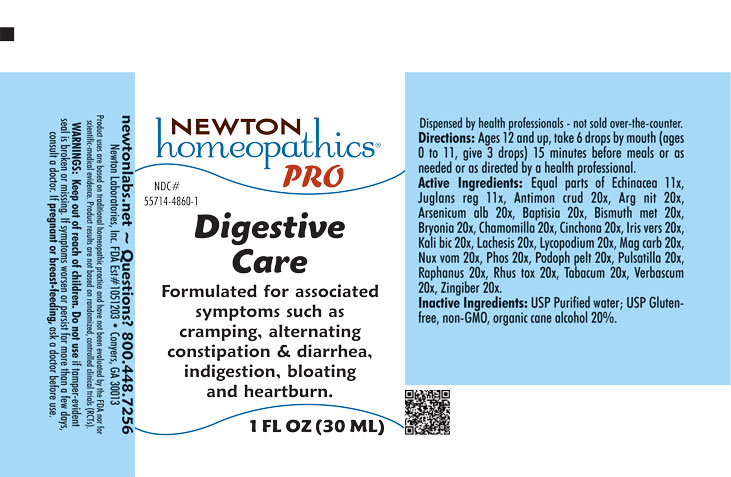 DRUG LABEL: Digestive Care
NDC: 55714-4860 | Form: LIQUID
Manufacturer: Newton Laboratories, Inc.
Category: homeopathic | Type: HUMAN OTC DRUG LABEL
Date: 20251201

ACTIVE INGREDIENTS: BISMUTH 20 [hp_X]/1 mL; ANTIMONY TRISULFIDE 20 [hp_X]/1 mL; SILVER NITRATE 20 [hp_X]/1 mL; ARSENIC TRIOXIDE 20 [hp_X]/1 mL; BAPTISIA TINCTORIA ROOT 20 [hp_X]/1 mL; BRYONIA ALBA ROOT 20 [hp_X]/1 mL; MATRICARIA CHAMOMILLA 20 [hp_X]/1 mL; CINCHONA OFFICINALIS BARK 20 [hp_X]/1 mL; IRIS VERSICOLOR ROOT 20 [hp_X]/1 mL; POTASSIUM DICHROMATE 20 [hp_X]/1 mL; LACHESIS MUTA VENOM 20 [hp_X]/1 mL; LYCOPODIUM CLAVATUM SPORE 20 [hp_X]/1 mL; MAGNESIUM CARBONATE 20 [hp_X]/1 mL; STRYCHNOS NUX-VOMICA SEED 20 [hp_M]/1 mL; PHOSPHORUS 20 [hp_X]/1 mL; PODOPHYLLUM 20 [hp_X]/1 mL; ANEMONE PULSATILLA 20 [hp_X]/1 mL; RADISH 20 [hp_X]/1 mL; TOXICODENDRON PUBESCENS LEAF 20 [hp_X]/1 mL; TOBACCO LEAF 20 [hp_X]/1 mL; VERBASCUM THAPSUS 20 [hp_X]/1 mL; GINGER 20 [hp_X]/1 mL; ECHINACEA, UNSPECIFIED 11 [hp_X]/1 mL; JUGLANS REGIA LEAF 11 [hp_X]/1 mL
INACTIVE INGREDIENTS: WATER; ALCOHOL

Digestive 4860L

INDICATIONS & USAGE SECTION

Formulated for associated symptoms such as cramping, alternating constipation & diarrhea, indigestion, bloating and heartburn.

DOSAGE & ADMINISTRATION SECTION

Directions: Ages 12 and up, take 6 drops by mouth (ages 0 to 11, give 3 drops) 15 minutes before meals or as needed or as directed by a health professional.

OTC - ACTIVE INGREDIENT SECTION

Equal parts of Echinacea 11x, Juglans reg 11x, Antimon crud 20x, Arg nit 20x, Arsenicum alb 20x, Baptisia 20x, Bismuth met 20x, Bryonia 20x, Chamomilla 20x, Cinchona 20x, Iris vers 20x, Kali bic 20x, Lachesis 20x, Lycopodium 20x, Mag carb 20x, Nux vom 20x, Phos 20x, Podoph pelt 20x, Pulsatilla 20x, Raphanus 20x, Rhus tox 20x, Tabacum 20x, Verbascum 20x, Zingiber 20x.

OTC - PURPOSE SECTION

Formulated for associated symptoms such as crampting, alternating constipation & diarrhea, indigestion, bloating and heartburn.

INACTIVE INGREDIENT SECTION

Inactive Ingredients: USP Purified Water; USP Gluten-free, non-GMO, organic cane alcohol 20%.

QUESTIONS SECTION

newtonlabs.net – Questions? 800.448.7256

Newton Laboratories, Inc. FDA Est # 1051203 - Conyers, GA 30013

WARNINGS SECTION

WARNINGS: Keep out of reach of children. Do not use if tamper-evident seal is broken or missing. If symptoms worsen or persist for more than a few days, consult a doctor. If pregnant or breast-feeding, ask a doctor before use.

OTC - PREGNANCY OR BREAST FEEDING SECTION

If pregnant or breast feeding, ask a doctor before use.

OTC - KEEP OUT OF REACH OF CHILDREN SECTION

Keep out of reach of children.